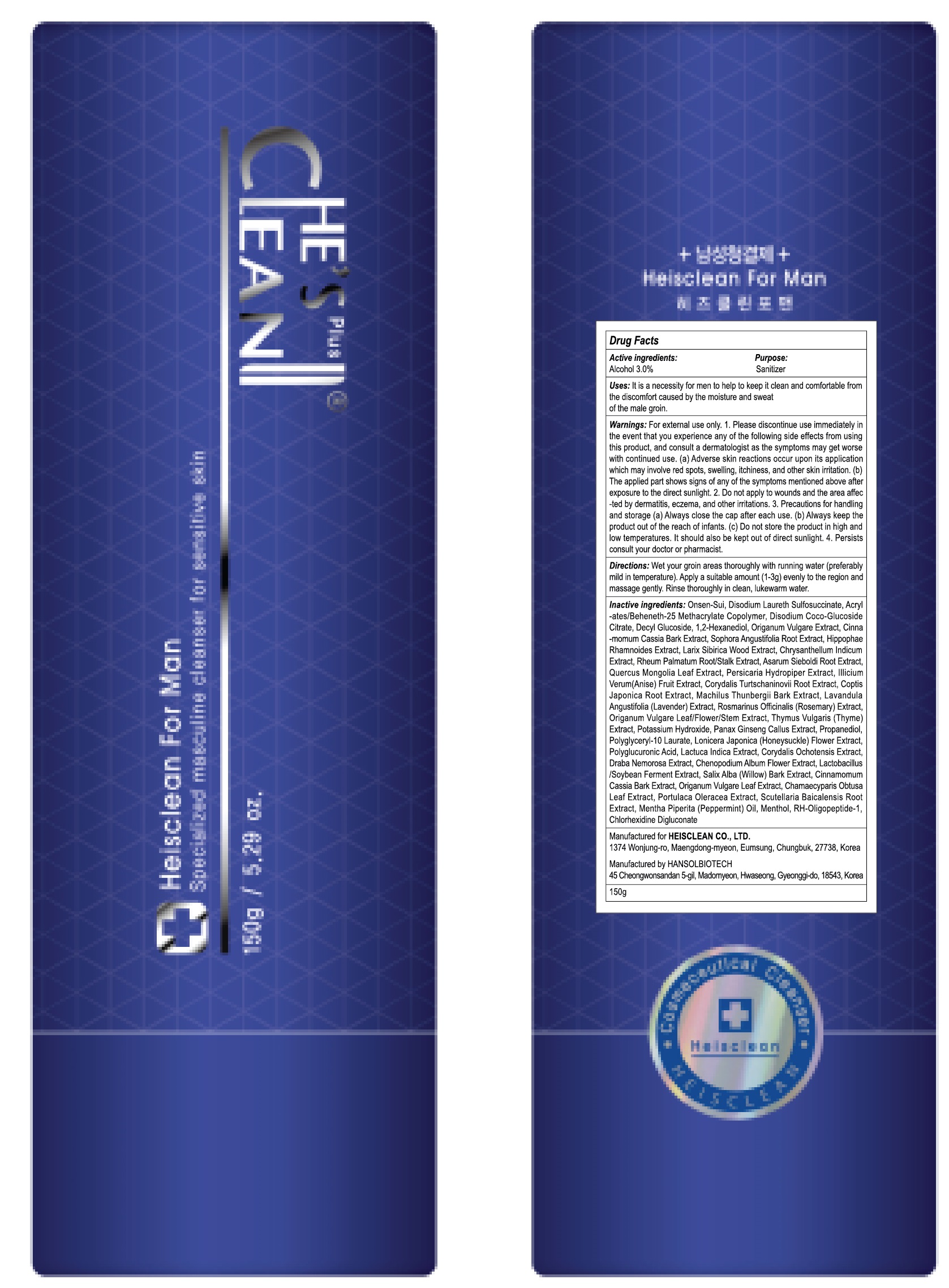 DRUG LABEL: HEISCLEAN FOR MAN
NDC: 42979-150 | Form: GEL
Manufacturer: HEISCLEAN.CO.,LTD
Category: otc | Type: HUMAN OTC DRUG LABEL
Date: 20171208

ACTIVE INGREDIENTS: Alcohol 6 g/200 g
INACTIVE INGREDIENTS: Water; Disodium Laureth Sulfosuccinate

ACTIVE INGREDIENT

Active Ingredient: Alcohol 3.0%

INACTIVE INGREDIENT

Inactive Ingredients: Onsen-Sui, Disodium Laureth Sulfosuccinate, Acrylates/Beheneth-25 Methacrylate Copolymer, Disodium Coco-Glucoside Citrate, Decyl Glucoside, 1,2-Hexanediol, Origanum Vulgare Extract, Cinnamomum Cassia Bark Extract, Sophora Angustifolia Root Extract, Hippophae Rhamnoides Extract, Larix Sibirica Wood Extract, Chrysanthellum Indicum Extract, Rheum Palmatum Root/Stalk Extract, Asarum Sieboldi Root Extract, Quercus Mongolia Leaf Extract, Persicaria Hydropiper Extract, Illicium Verum (Anise) Fruit Extract, Corydalis Turtschaninovii Root Extract, Coptis Japonica Root Extract, Machilus Thunbergii Bark Extract, Lavandula Angustifolia (Lavender) Extract, Rosmarinus Officinalis (Rosemary) Extract, Origanum Vulgare Leaf/Flower/Stem Extract, Thymus Vulgaris (Thyme) Extract, Potassium Hydroxide, Panax Ginseng Callus Extract, Propanediol, Polyglyceryl-10 Laurate, Lonicera Japonica (Honeysuckle) Flower Extract, Polyglucuronic Acid, Lactuca Indica Extract, Corydalis Ochotensis Extract, Draba Nemorosa Extract, Chenopodium Album Flower Extract, Lactobacillus/Soybean Ferment Extract, Salix Alba (Willow) Bark Extract, Cinnamomum Cassia Bark Extract, Origanum Vulgare Leaf Extract, Chamaecyparis Obtusa Leaf Extract, Portulaca Oleracea Extract, Scutellaria Baicalensis Root Extract, Mentha Piperita (Peppermint) Oil, Menthol, RH-Oligopeptide-1, Chlorhexidine Digluconate

PURPOSE

Purpose: Sanitizer

WARNINGS

For external use only

1. Please discontinue use immediately in the event that you experience any of the following side effects from using this product, and consult a dermatologist as the symptoms may get worse with continued use. (a) Adverse skin reactions occur upon its application which may involve red spots, swelling, itchiness, and other skin irritation. (b) The applied part shows signs of any of the symptoms mentioned above after exposure to the direct sunlight.

2. Do not apply to wounds and the area affected by dermatitis, eczema, and other irritations.

3. Precautions for handling and storage (a) Always close the cap after each use. (b) Always keep the product out of the reach of infants. (c) Do not store the product in high and low temperatures. It should also be kept out of direct sunlight.

4. Persists consult your doctor or pharmacist.

KEEP OUT OF REACH OF CHILDREN

Always keep the product out of the reach of infants.

Uses

It is a necessity for men to help to keep it clean and comfortable from the discomfort caused by the moisture and sweat of the male groin.

Directions

Wet your groin areas thoroughly with running water (preferably mild in temperature). Apply a suitable amount (1-3g) evenly to the region and massage gently. Rinse thoroughly in clean, lukewarm water.